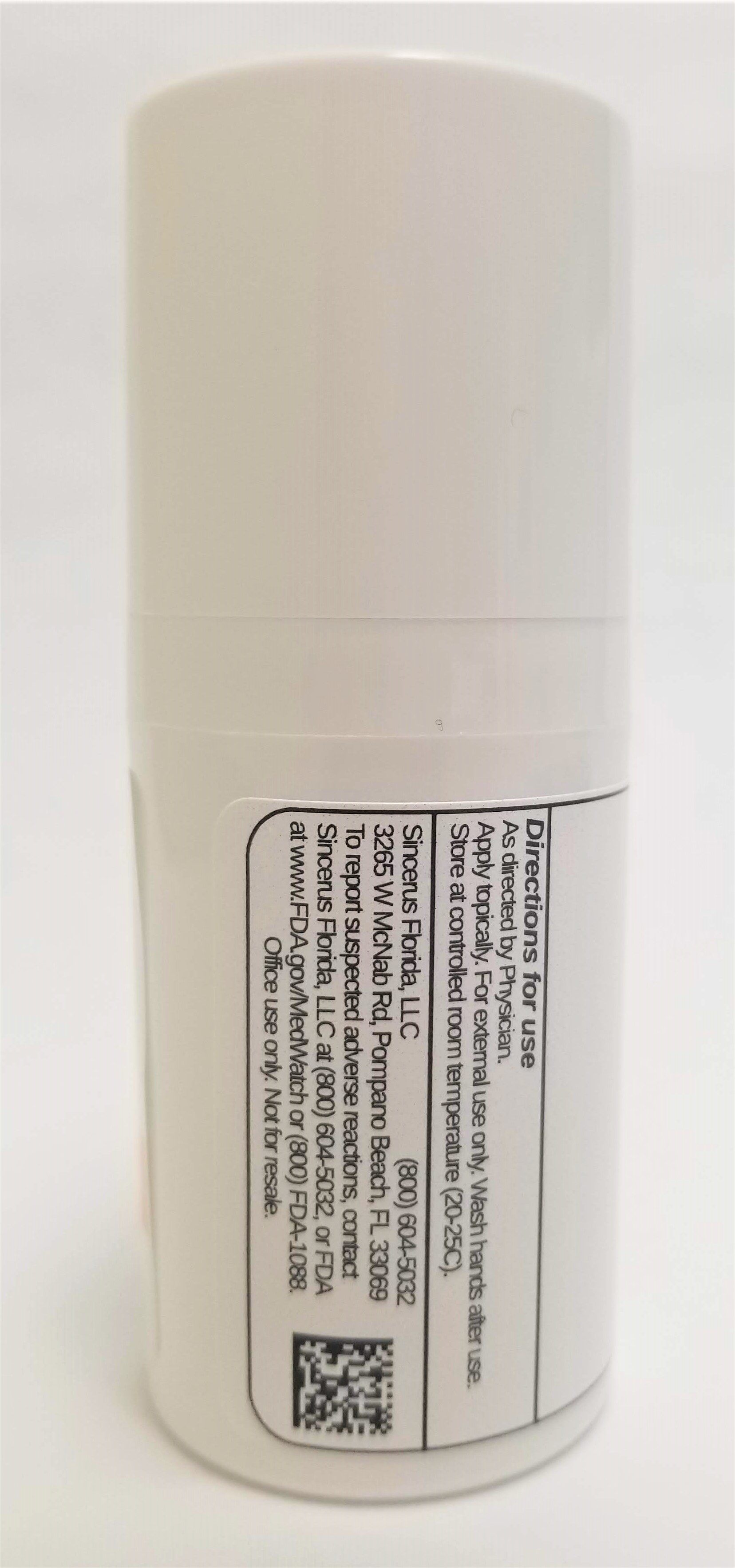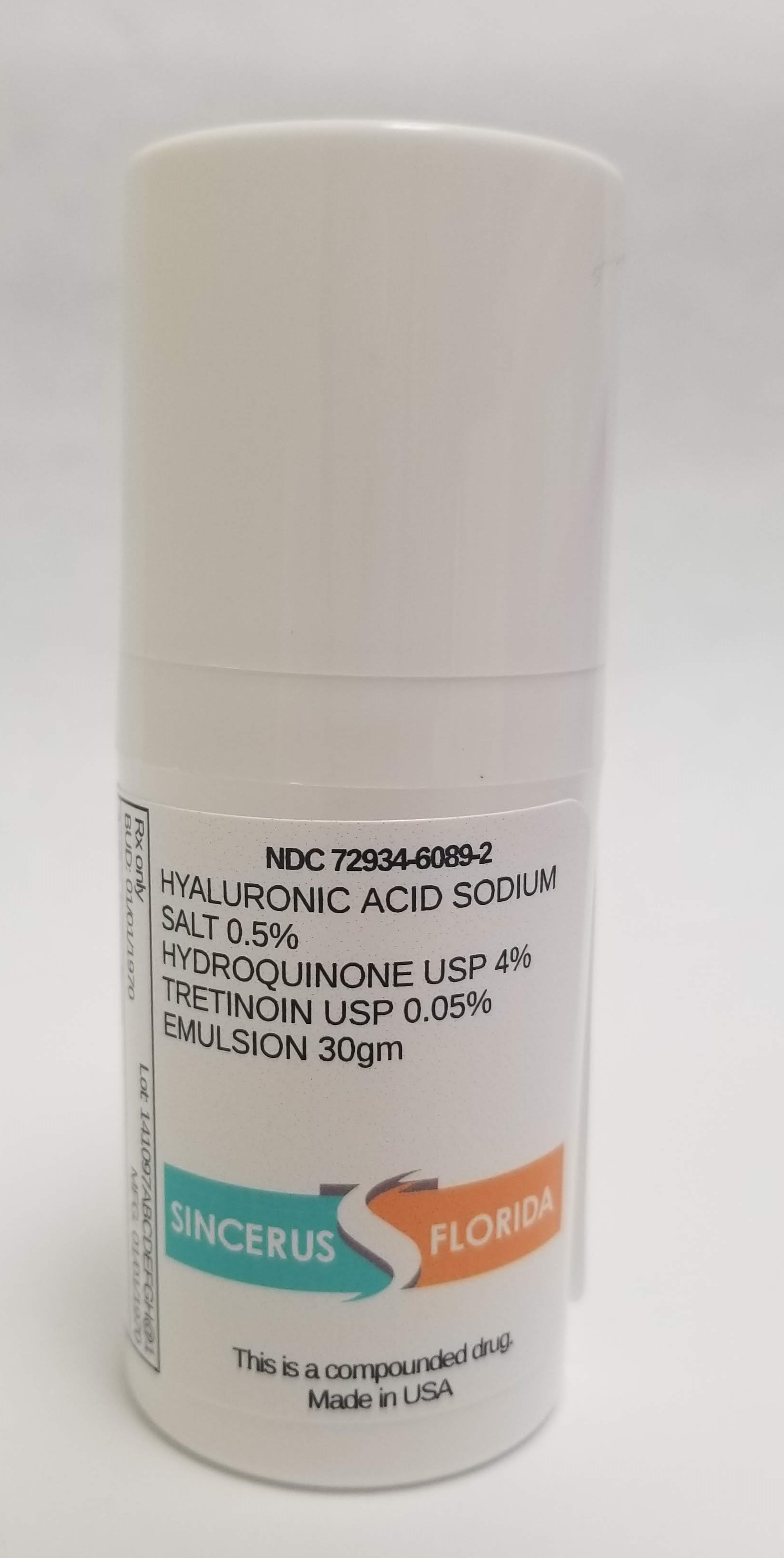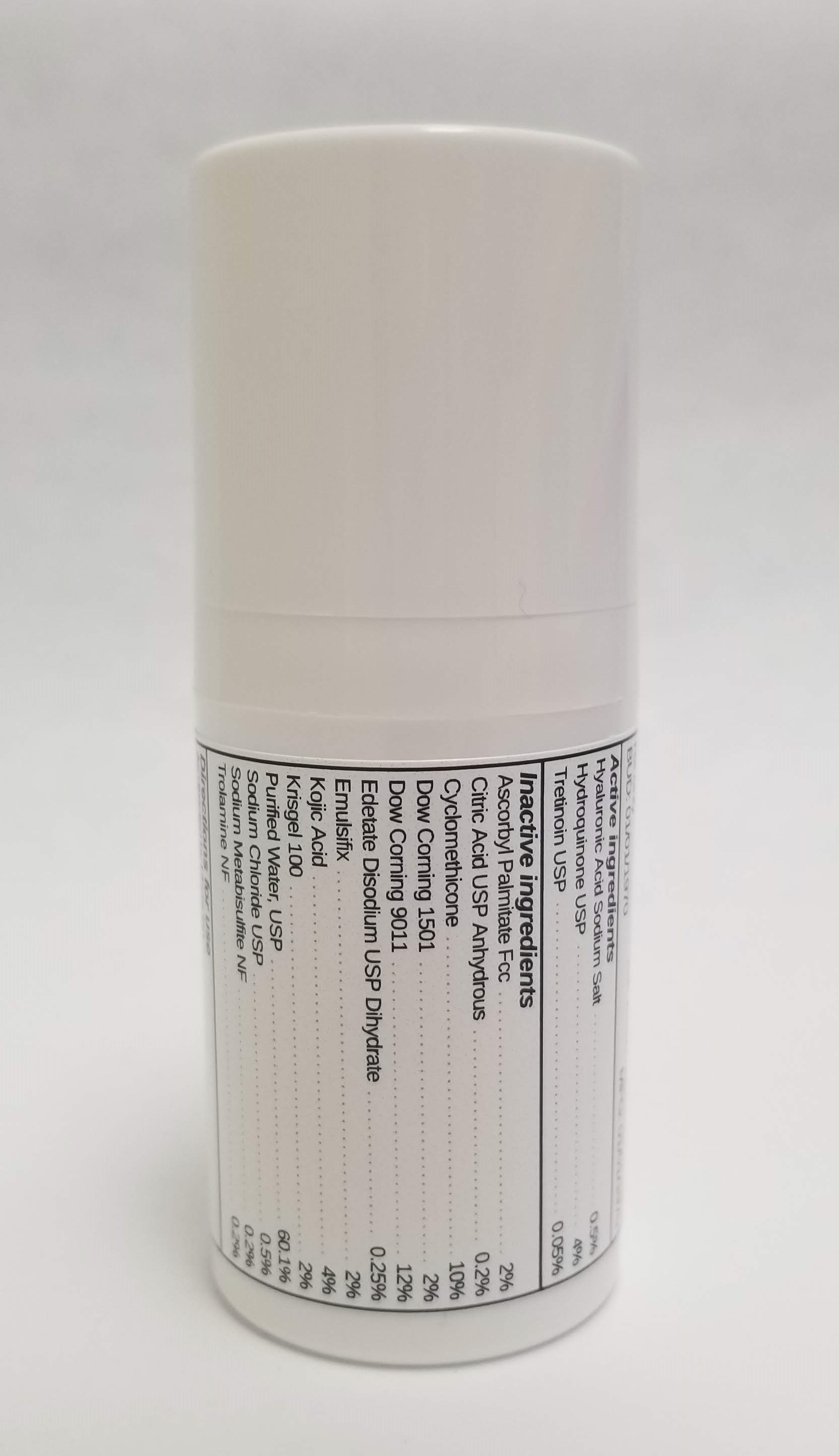 DRUG LABEL: HYALURONIC ACID SODIUM SALT 0.5% / HYDROQUINONE 4%  / TRETINOIN 0.05%
NDC: 72934-6089 | Form: EMULSION
Manufacturer: Sincerus Florida, LLC
Category: prescription | Type: HUMAN PRESCRIPTION DRUG LABEL
Date: 20190517

ACTIVE INGREDIENTS: HYALURONATE SODIUM 0.5 g/100 g; TRETINOIN 0.05 g/100 g; HYDROQUINONE 4 g/100 g

HYALURONIC ACID SODIUM SALT 0.5% / HYDROQUINONE 4% / TRETINOIN 0.05%